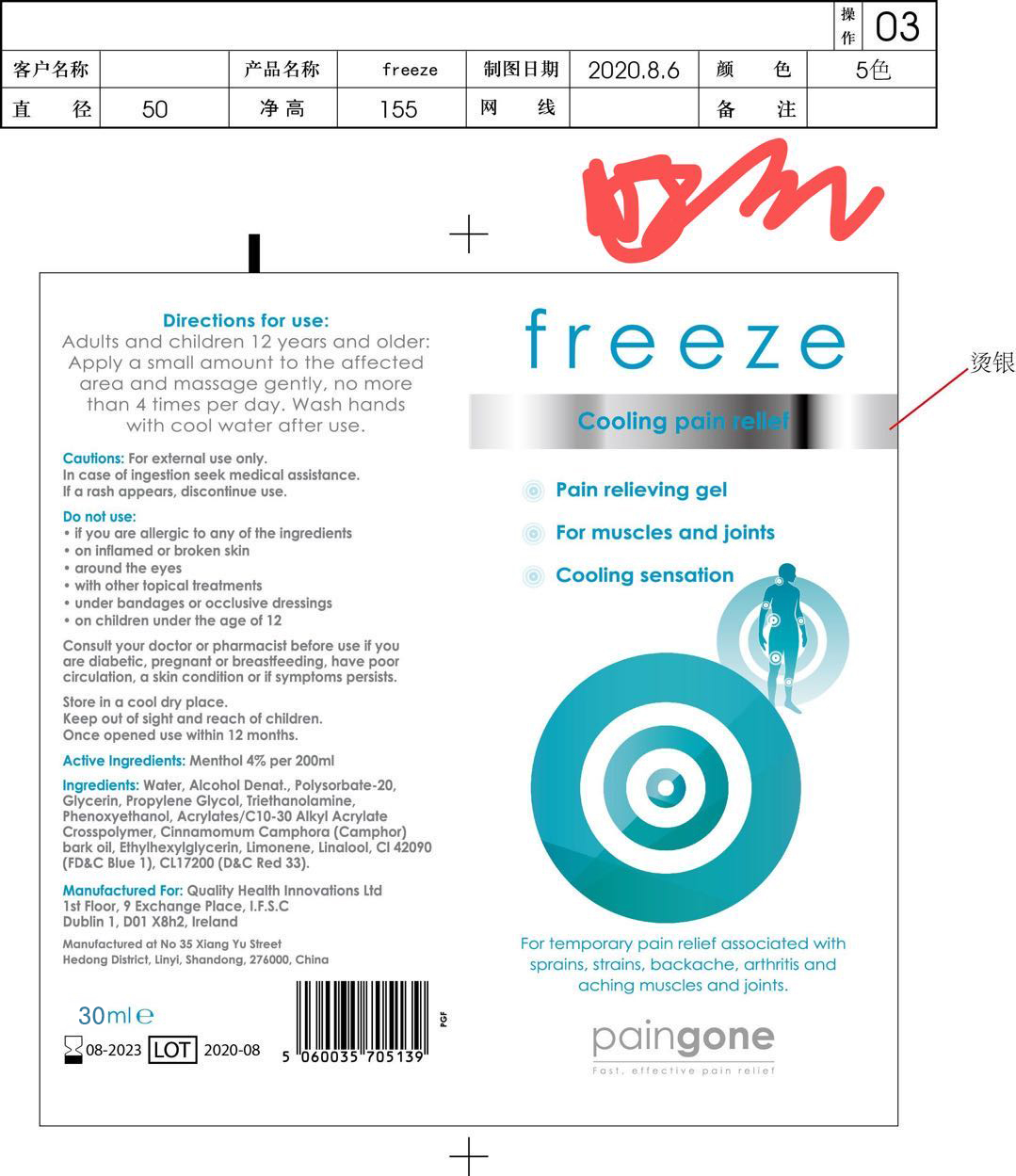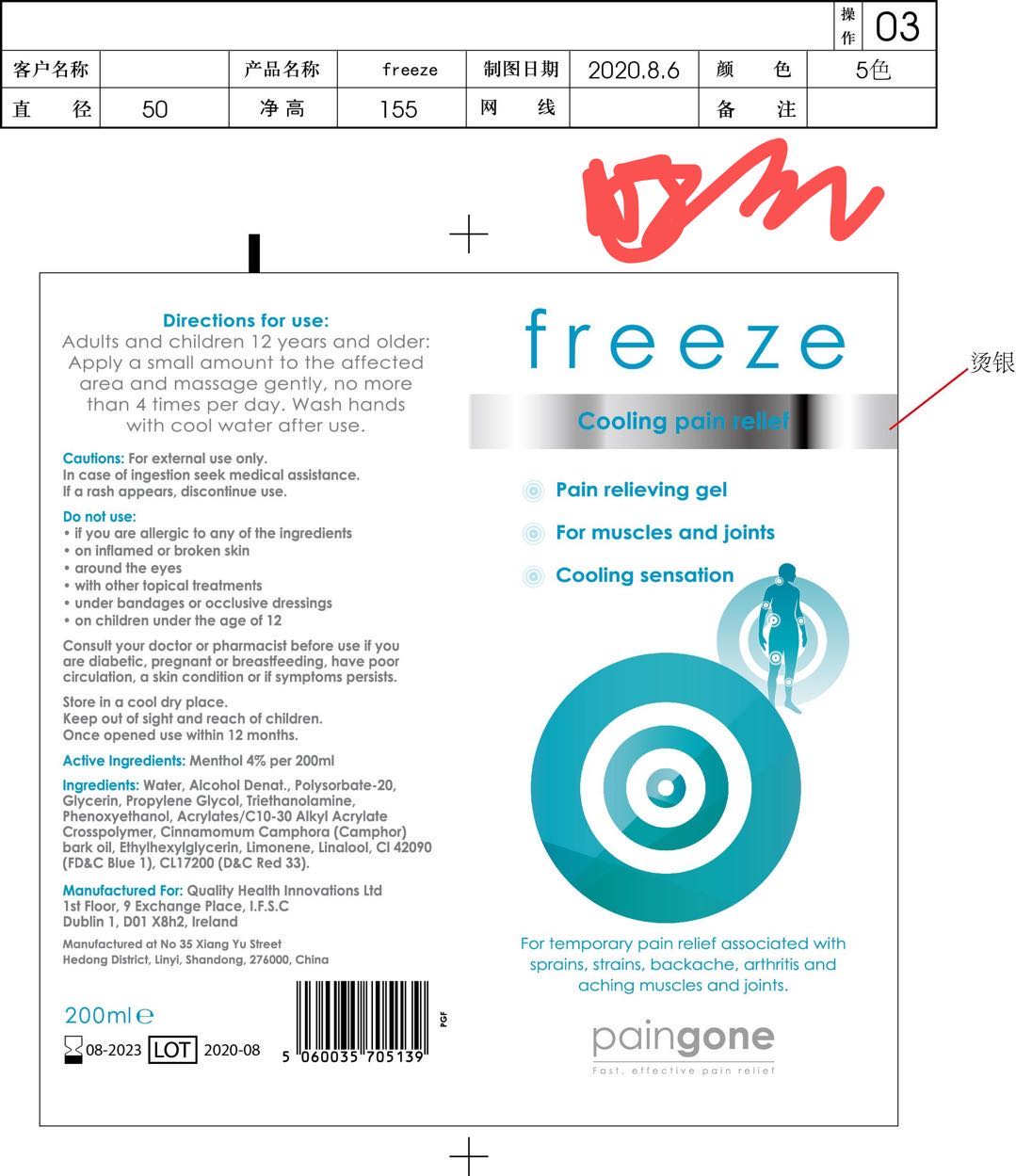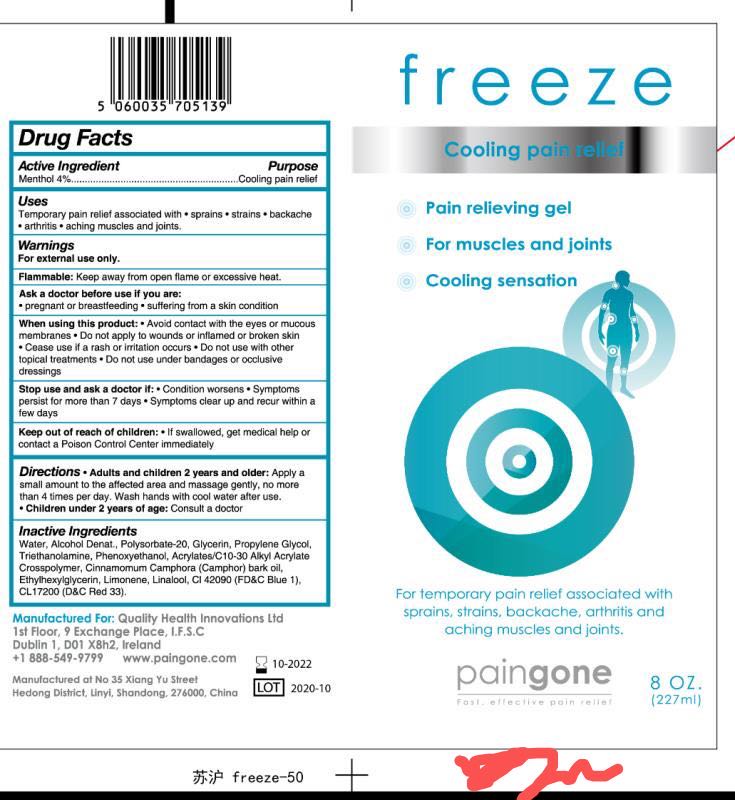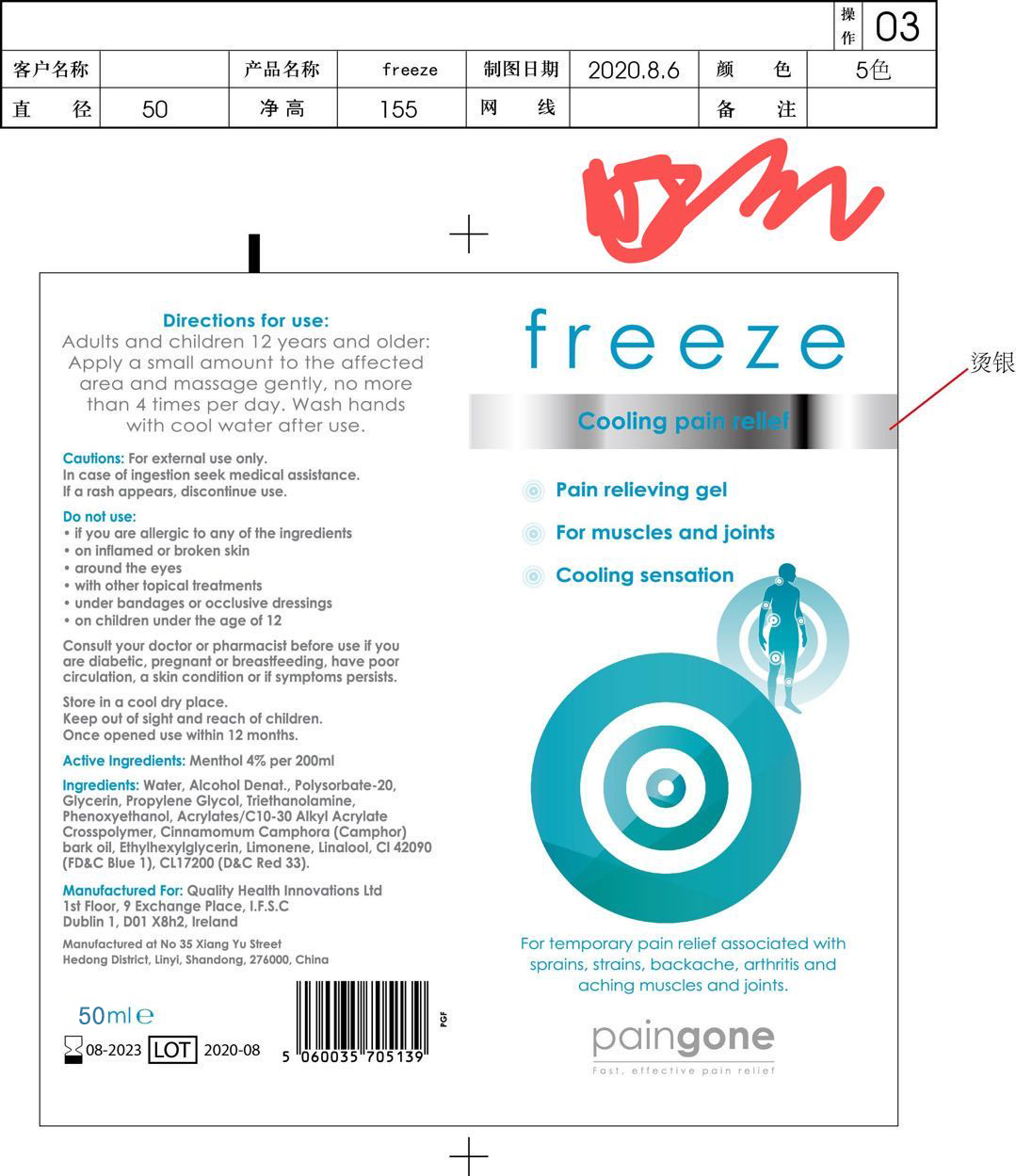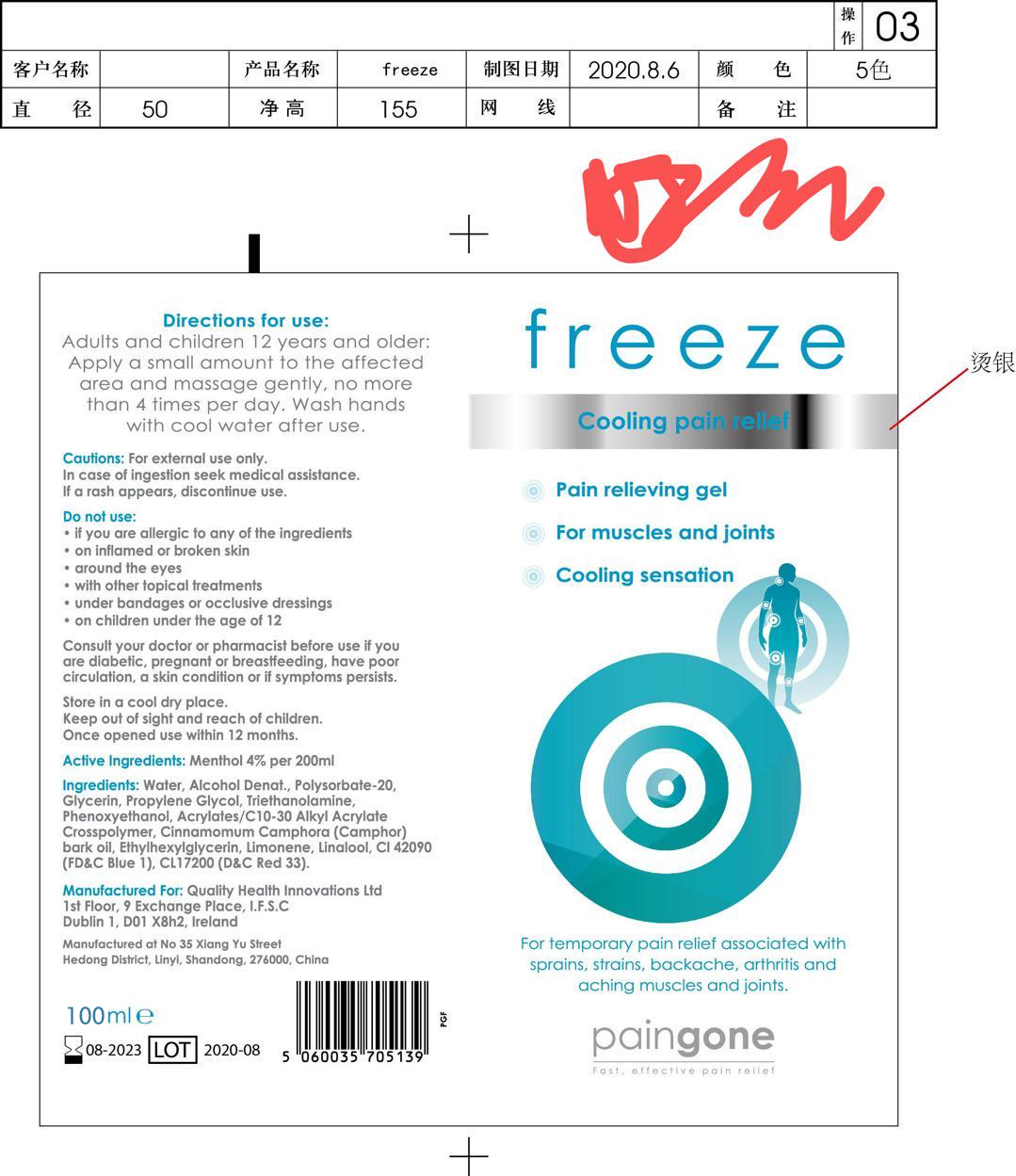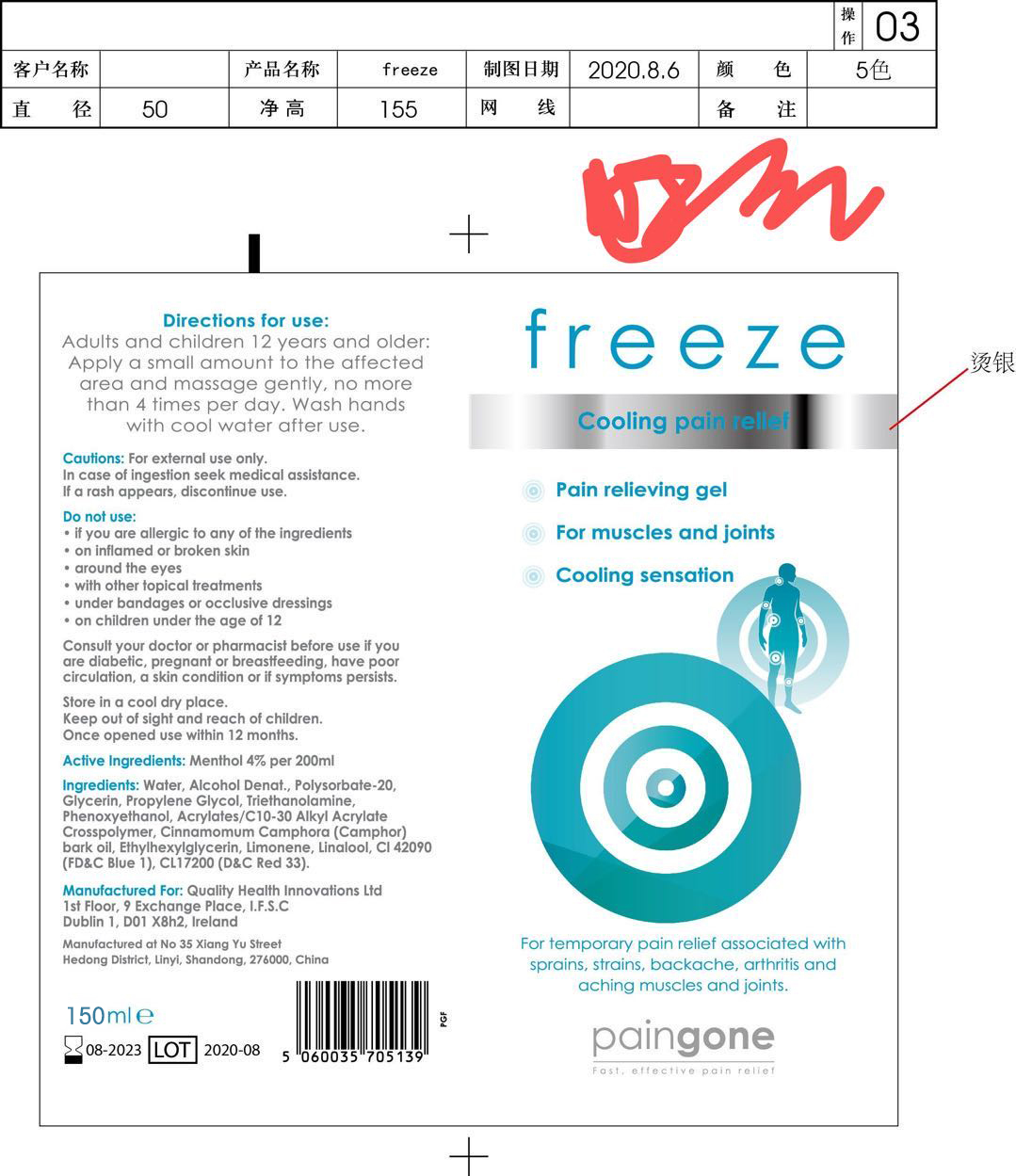 DRUG LABEL: FREEZE COOLING PAIN RELIEF
NDC: 69980-102 | Form: GEL
Manufacturer: Shandong Vianor Healthy Science Co.,Ltd.
Category: otc | Type: HUMAN OTC DRUG LABEL
Date: 20210125

ACTIVE INGREDIENTS: MENTHOL 4 g/100 mL
INACTIVE INGREDIENTS: CARBOMER INTERPOLYMER TYPE A (55000 CPS); LINALOOL, (+/-)-; D&C RED NO. 33; ALCOHOL; POLYSORBATE 20; WATER; GLYCERIN; CAMPHOR OIL; LIMONENE, (+)-; TROLAMINE; ETHYLHEXYLGLYCERIN; PROPYLENE GLYCOL; PHENOXYETHANOL; FD&C BLUE NO. 1

69980-102
FREEZE COOLING PAIN RELIEF

Active Ingredient(s)

Menthol 4%

Purpose

/

Use

Adults and children 12 years and older: Apply a small amount to the affected area and massage gently, no more han 4 times per day. Wash hands with cool water after use.

Warnings

for external use only.
In cose of Ingestion seek medical assistance.
If a rash appears, dis.continue use.

Do not use

If you are allerglc to any of the ingredients, on inflamed or broken skin around the eyes with other topical treatments under bandages or occlusive dressings on children under the age of 12

WHEN USING

If you are allerglc to any of the ingredients, on inflamed or broken skin around the eyes with other topical treatments under bandages or occlusive dressings on children under the age of 12

STOP USE

Consult your doctor or pharmacist before use if you are diabetic, pregnant or breastfeeding. have poor circulation, a skin condition or if symptoms persists.

Directions

Adults and children 12 years and older: Apply a small amount to the affected area and massage gently, no more han 4 times per day. Wash hands with cool water after use.

Inactive ingredients

Water, Alcohol Denat., Polysorbate-20, Glycerin, Propylene Glycol, Triethanolamine, Phenoxyethanol, Acrylates/ C10-30 Alkyl Acrylate Crosspolymer. Cinnamomum Camphora (Camphor) bark oil, Ethylhexylglycerin, limonene, Linalool, Cl42090 (FD&C Blue 1), CL17200 (D&C Red 33).

Package Label - Principal Display Panel

69980-102-05 200ml

69980-102-04 150ml

69980-102-02 50ml

69980-102-01 30ml

69980-102-03 100ml

69980-102-06 30ml

69980-102-07 50ml

69980-102-08 100ml

69980-102-09 150ml

69980-102-010 200ml

69980-102-011 227ml